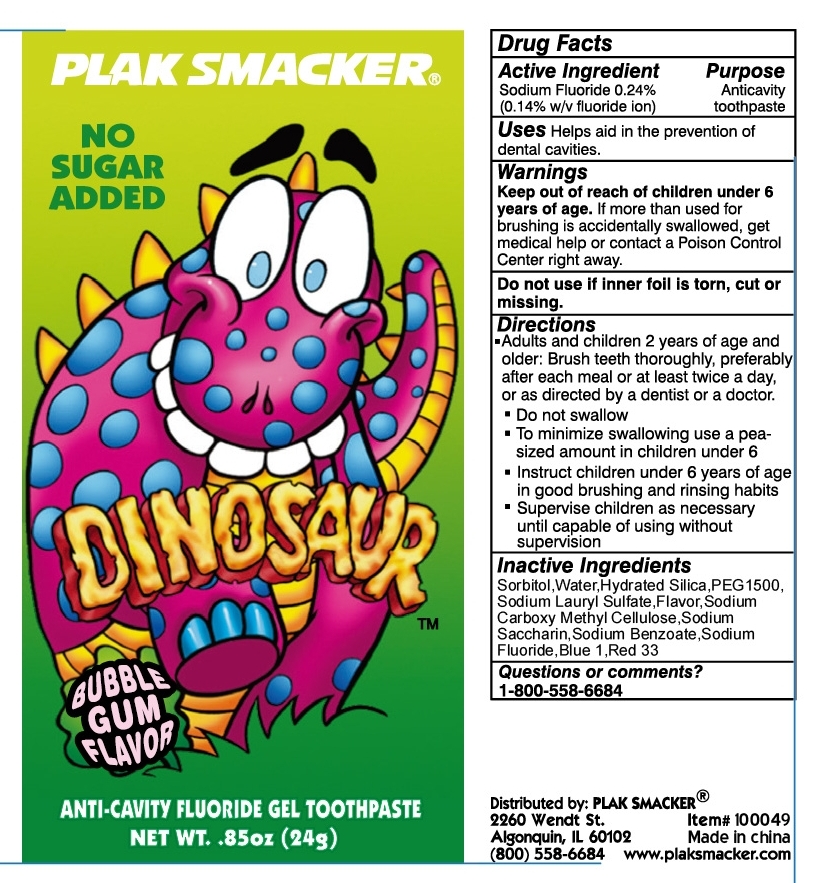 DRUG LABEL: Plak Smacker Anti Cavity Fluoride
NDC: 71035-700 | Form: PASTE
Manufacturer: Yangzhou Hongshengding Chemical Co.,Ltd.
Category: otc | Type: HUMAN OTC DRUG LABEL
Date: 20180106

ACTIVE INGREDIENTS: SODIUM FLUORIDE 0.24 g/100 g
INACTIVE INGREDIENTS: SORBITOL; HYDRATED SILICA; DISODIUM ETHYLENE DIMYRISTAMIDE PEG-15 DISULFATE; SACCHARIN SODIUM; SODIUM BENZOATE; WATER; DISODIUM CARBOXYMETHYLARSONATE; SODIUM LAURYL SULFATE

Plak Smacker DINOSAUR ANTI-CAVITY FLUORIDE GEL TOOTHPASTE

Active ingredients

Sodium Fluoride 0.24%(0.14% w/v Fluoride ion)

Purpose

anticavity toothpaste

Uses

help aids in the prevention of dental cavities.

Warnings

Keep out of the reach of children under 6 years of age.if more than used for brushing is accidentally swalowed, get medical help or contact a Poison Control Center right away.

Keep out of reach of children.

Directions

Adults and children 2years of age and older:Brush teeth thoroughly,preferably after each meal or at least twice a day,or as directed by a dentist or a doctor.

Do not swallow

to minimize swallowing use a peasized amount in children under 6

instruct children under 6 years oa age in good brushing and rinsing habits.

supervise children as necessary until capable of useing without supervision

INACTIVE INGREDIENT

Sorbitol,Water ,Hydreated silica,PEG1500,Sodium Lauryl Sulfate,Flavor ,Sodium Carboxy Methyl Cellulose ,Sodium Saccharin,Sodium Benzoate,Blue1